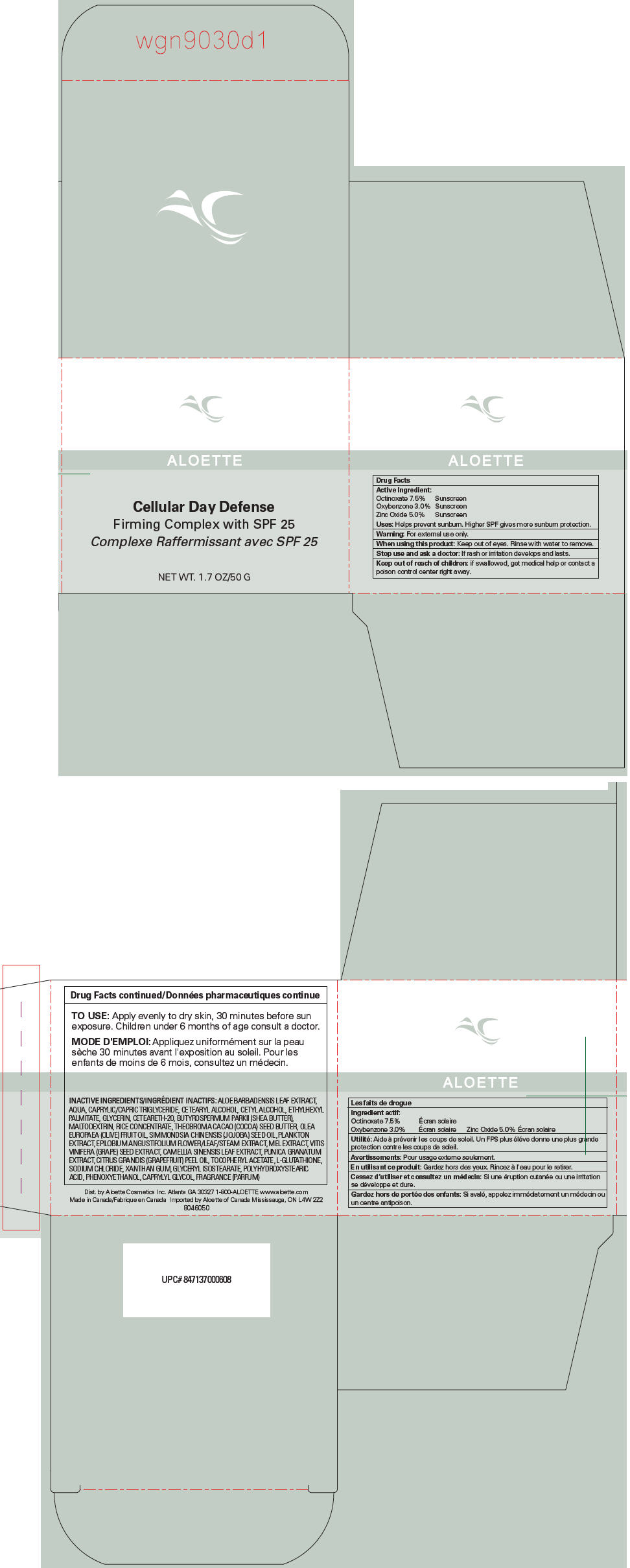 DRUG LABEL: Cellular Day Defense Firming SPF 25
NDC: 65447-050 | Form: CREAM
Manufacturer: Aloette Cosmetics Inc.
Category: otc | Type: HUMAN OTC DRUG LABEL
Date: 20121220

ACTIVE INGREDIENTS: ZINC OXIDE 5.0 g/100 g; OXYBENZONE 3.0 g/100 g; OCTINOXATE 7.5 g/100 g
INACTIVE INGREDIENTS: ALOE VERA LEAF; WATER; TRICAPRYLIN; CETOSTEARYL ALCOHOL; CETYL ALCOHOL; ETHYLHEXYL PALMITATE; GLYCERIN; POLYOXYL 20 CETOSTEARYL ETHER; .ALPHA.-TOCOPHEROL ACETATE; SODIUM CHLORIDE; XANTHAN GUM; GLYCERYL ISOSTEARATE; PHENOXYETHANOL; CAPRYLYL GLYCOL

ALOETTE
Cellular Day Defense

Drug Facts

ACTIVE INGREDIENT

Active Ingredient
Octinoxate 7.5% | Sunscreen
Oxybenzone 3.0% | Sunscreen
Zinc Oxide 5.0% | Sunscreen

Uses

Helps prevent sunburn. Higher SPF gives more sunburn protection.

Warning

For external use only.

When using this product

Keep out of eyes. Rinse with water to remove.

Stop use and ask a doctor

If rash or irritation develops and lasts.

Keep out of reach of children: if swallowed, get medical help or contact a poison control center right away.

TO USE

Apply evenly to dry skin, 30 minutes before sun exposure. Children under 6 months of age consult a doctor.

INACTIVE INGREDIENTS

ALOE BARBADENSIS LEAF EXTRACT, AQUA, CAPRYLIC/CAPRIC TRIGLYCERIDE, CETEARYL ALCOHOL, CETYL ALCOHOL, ETHYLHEXYL PALMITATE, GLYCERIN, CETEARETH-20, BUTYROSPERMUM PARKII (SHEA BUTTER), MALTODEXTRIN, RICE CONCENTRATE, THEOBROMA CACAO (COCOA) SEED BUTTER, OLEA EUROPAEA (OLIVE) FRUIT OIL, SIMMONDSIA CHINENSIS (JOJOBA) SEED OIL, PLANKTON EXTRACT, EPILOBIUM ANGUSTIFOLIUM FLOWER/LEAF/STEAM EXTRACT, MEL EXTRACT, VITIS VINIFERA (GRAPE) SEED EXTRACT, CAMELLIA SINENSIS LEAF EXTRACT, PUNICA GRANATUM EXTRACT, CITRUS GRANDIS (GRAPEFRUIT) PEEL OIL, TOCOPHERYL ACETATE, L-GLUTATHIONE, SODIUM CHLORIDE, XANTHAN GUM, GLYCERYL ISOSTEARATE, POLYHYDROXYSTEARIC ACID, PHENOXYETHANOL, CAPRYLYL GLYCOL, FRAGRANCE (PARFUM)

Dist. by Aloette Cosmetics Inc. Atlanta GA 30327

PRINCIPAL DISPLAY PANEL - 50 g Jar Carton

ALOETTE

Cellular Day Defense
Firming Complex with SPF 25

NET WT. 1.7 OZ/50 G